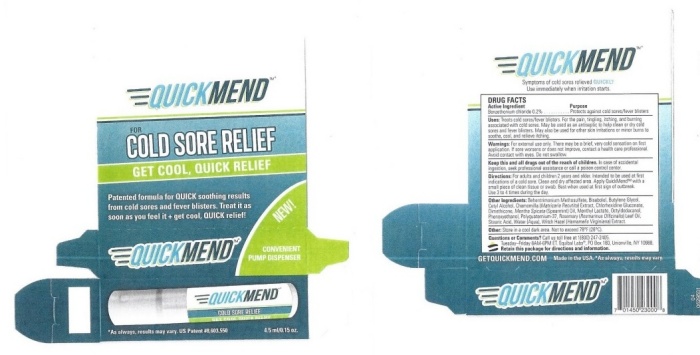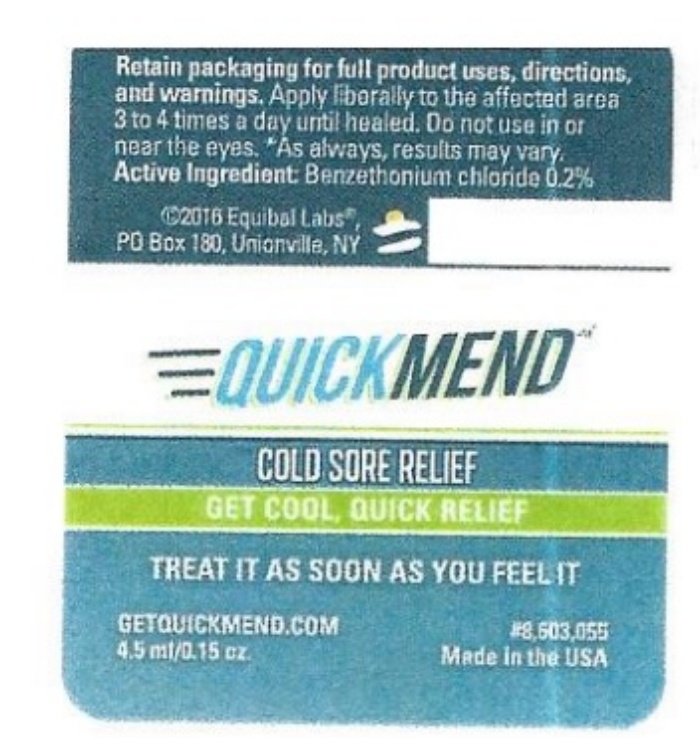 DRUG LABEL: QuickMend
NDC: 53228-230 | Form: LIQUID
Manufacturer: Equibal, Inc.
Category: otc | Type: HUMAN OTC DRUG LABEL
Date: 20251217

ACTIVE INGREDIENTS: BENZETHONIUM CHLORIDE 0.09 mg/9 mL
INACTIVE INGREDIENTS: BEHENTRIMONIUM METHOSULFATE; LEVOMENOL; BUTYLENE GLYCOL; CETYL ALCOHOL; CHAMOMILE; CHLORHEXIDINE GLUCONATE; DIMETHICONE; SPEARMINT; MENTHYL LACTATE, (-)-; OCTYLDODECANOL; PHENOXYETHANOL; POLYQUATERNIUM 37 (200 MPA.S); ROSEMARY OIL; STEARIC ACID; WATER; HAMAMELIS VIRGINIANA TOP

QuickMend - 230

DRUG FACTS Active Ingredient

Benzethonium chloride 0.2%

Purpose

Protect against cold sore/fever blisters.

Keep out of reach of children

Keep this and all drugs out of the reach of children.

In case of accidental ingestion, seek professional assistance or call a poison control center.

Uses:

Treats cold sores/fever blisters. For the pain, tingling, itching, and burning associated with cold sores. May be used as an antiseptic to help clean or dry cold sores and fever blisters. May also be used for other skin irritations or minor burns to soothe, cool and relieve itching.

Warnings:

For external use only. There may be a brief, very cold sensation on first application. If sore worsens or does not improve, contact a health care professional. Avoid contact with eyes. Do not swallow.

Directions:

For adults and children 2 years and older. Intended to be used at first indications of a cold sore. Clean and dry affected area. Apply QuickMend™ with a small piece of clean tissue or swab. Best when used at first sign of outbreak. Use 3 to 4 times during the day.

Other Ingredients:

Behentrimonium Methosulfate, Bisabolol, Butylene Glycol, Cetyl Alcohol, Chamomilla (Matricaria Recutita) Extract, Chlorhexidine Gluconate, Dimethicone, Mentha Spicata (Spearmint) Oil, Menthyl Lactate, Octyldodecanol, Phenoxyethanol, Polyquaternium,-37, Rosemary(Rosmarinus Officinalis) Leaf Oil, Stearic Acid, Water (Aqua), Witch Hazel (Hamamelis Virginiana) Extract.

Questions or Comments? Other:

Call us toll free at 1 (800) 247-2405

Tuesday - Friday 8 a.m. - 6 p.m. EST.

Equibal Labs®, Unionville, NY 10988.

Retain this package for directions and information.

Other: Store in a cool dark area. Not to exceed 78°F (26°C)

QuickMend product label

QUICKMEND™; FOR; COLD SORE RELIEF; GET COOL, QUICK RELIEF; Patented formula for QUICK soothing results from cold sores and fever blisters. Treat it as soon as you feel it + get cool, QUICK relief!; QUICKMEND™ | NEW!; CONVENIENT PUMP DISPENSER | DRUG FACTS; Active Ingredient Purpose; Benzethonium Chloride 0.2% w/w Protects against cold; sores/fever blisters; Uses:Treats cold sores/fever blisters. For the pain, tingling, itching, and burning associated with cold sores. May be used as an antiseptic to help clean or dry cold sores and fever blisters. May also be used for other skin irritations or minor burns to soothe, cool, and relieve itching.; Warnings: For external use only. There may be a brief, very cold sensation on first application. If sore worsens or does not improve, contact a health care professional. Avoid contact with eyes. Do not swallow.; Keep this and all drugs out of the reach of children. In case of accidental ingestion, seek professional assistance or call poison control center.; Directions:For adults and children 2 years and older. Intended to be used at first indications of a cold sore. Clean and dry affected area. Apply QuickMend™ with a small piece of clean tissue or swab. Best when used at first signe of outbreak. Use 3 to 4 times during the day.; Other Ingredients:; Behentrimonium Methosulfate, Bisabolol, Butylene Glycol, Cetyl Alcohol, Chamomilla (Matricaria Recutita) Extract, Chlorhexidine Gluconate, Dimethicone, Mentha Spicata (Spearmint) Oil, Menthyl Lactate, Octylodecanol, Phenoxyethanol, Polyquaterniuim-37, Rosemary (Rosmarinus Officinalist) Leaf Oil, Stearic Acid, Water (Aqua), Witch Hazel (Hamamelis Virginiana) Extract; Other:Store in a cool dark area. Not to exceed 78OF (26OC).; Questions or Comments?Call us toll free at 1(800)247-2405.; Tuesday – Friday 8AM-6PM ET. Equibal Labs®, PO Box 180,Unionville, NY 10988.; Retain this package for directions and information.
QUICKMEND™; COLD SORE RELIEF; *As always, results may vary. US Patent #8,603,550; 4.5 m./0.15oz. |  | GETQUICKMEND.COM Mad in the USA. *As always, results may vary.; QUICKMEND™